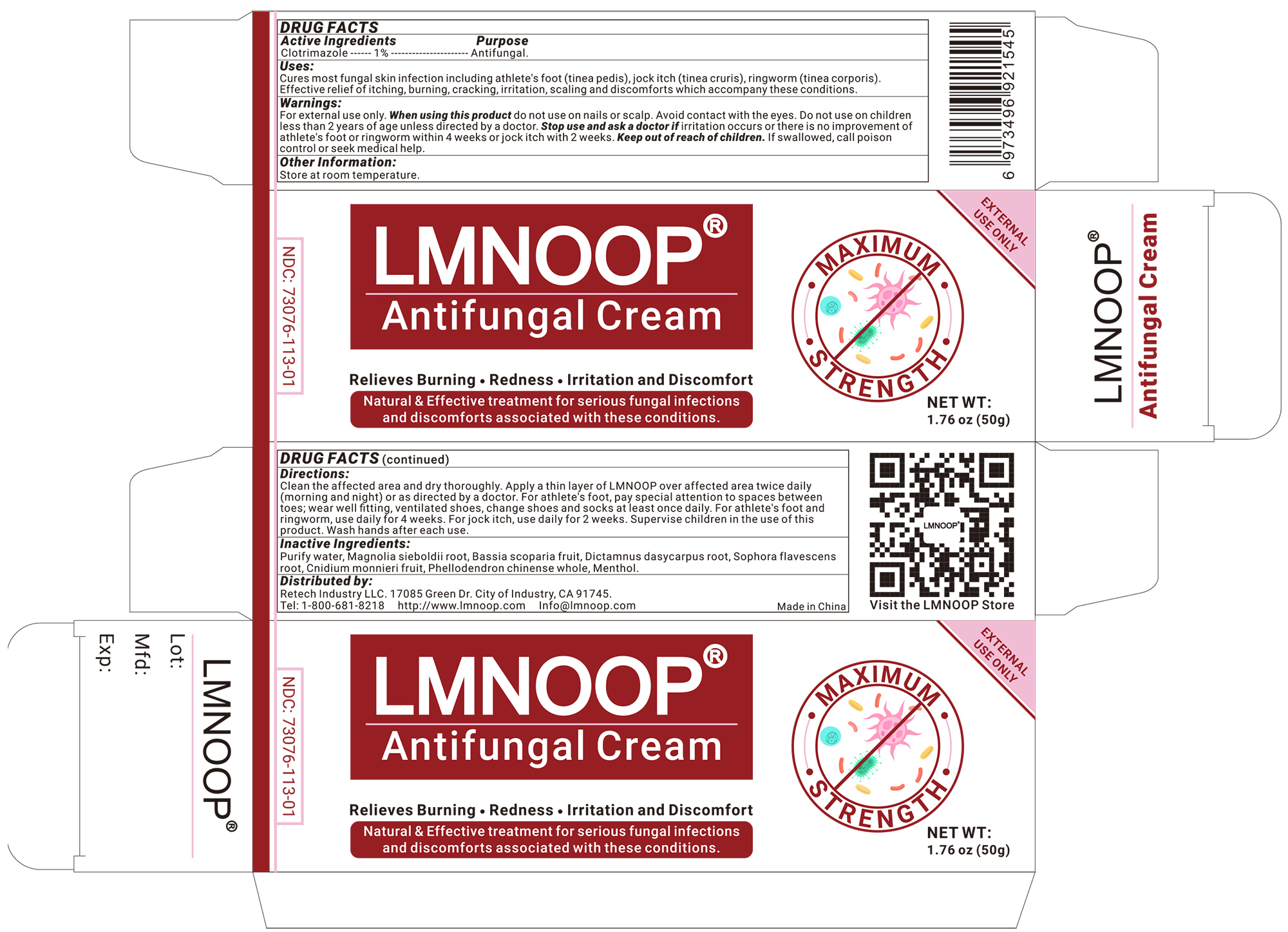 DRUG LABEL: LMNOOP Antifungal Cream
NDC: 73076-147 | Form: CREAM
Manufacturer: Shenzhen Ishan Technology Co., Ltd
Category: homeopathic | Type: HUMAN OTC DRUG LABEL
Date: 20260213

ACTIVE INGREDIENTS: OATMEAL 1 g/100 g
INACTIVE INGREDIENTS: MAGNOLIA SIEBOLDII ROOT 3 g/100 g; DICTAMNUS DASYCARPUS ROOT 3 g/100 g; PHELLODENDRON CHINENSE WHOLE 5 g/100 g; MENTHOL 1 g/100 g; BASSIA SCOPARIA FRUIT 3 g/100 g; SOPHORA FLAVESCENS ROOT 5 g/100 g; CNIDIUM MONNIERI FRUIT 3 g/100 g; WATER

Active ingredients

Serious Antifungal Cream

Inactive ingredients

Purify water, magnolia sieboldii root, bassia scoparia fruit, dictamnus dasycarpus root, sophora flavescens root, cnidium monnieri fruit, phellodendron chinense whole, menthol.

Keep out of reach of children.

If swallowed, call poison control or seek medical help.

Consulting a doctor before using

Use on children less than 2 years of age unless directed by a doctor.

Stop use and ask a doctor if

Irritation occurs or there is no improvement of athlete's foot or ringworm within 4 weeks or jock intch with 2 weeks.

USES

Cures most fungal skin infection including athlete's foot (tinea pedis), jock itch (tinea cruris), ringworm (tinea corporis). Effective relief of itching, burning, cracking, irritation, scaling and discomforts which accompany these conditions.

Other information

Store at room temperature.

Directions

* Clean the affected area and dry thoroughly
* Apply a thin layer of LMNOOP over affected area twice daily (morning and night) or as directed by a doctor.
* Use daily for 4 weeks, pay special attention to the spaces between the toes; wear well-fitting ventilated shoes, and change shoes and socks at least once daily.
* For athlete's foot, pay special attention to spaces between toes; wear well fitting, ventilated shoes, change shoes and socks at least once daily.
* For athlete's foot and ringworm, use daily for 4 weeks.
* For jock itch, use daily for 2 weeks.
* Supervise children in the use of this product.
* Wash hands after each use.

Dosage & administration

Apply as needed

When using this product

do not use on nails or scalp.

Warning

For external use only.